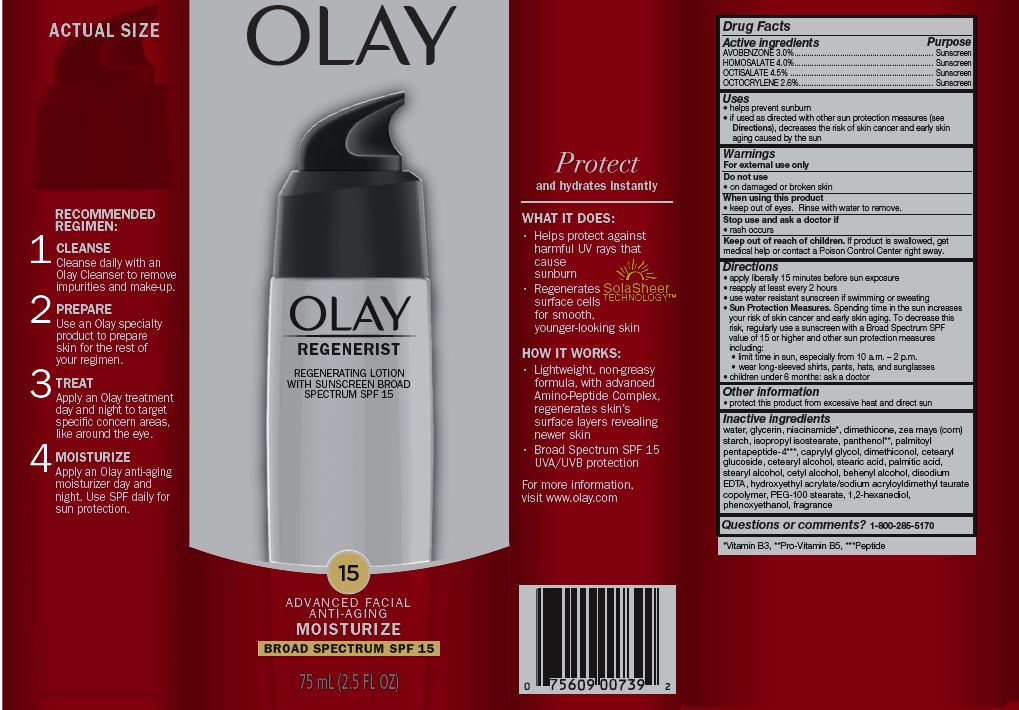 DRUG LABEL: Olay Regenerist Regenerating with Sunscreen Broad Spectrum SPF 15
NDC: 69423-719 | Form: LOTION
Manufacturer: The Procter & Gamble Manufacturing Company
Category: otc | Type: HUMAN OTC DRUG LABEL
Date: 20251218

ACTIVE INGREDIENTS: AVOBENZONE 3 g/100 mL; HOMOSALATE 4 g/100 mL; OCTISALATE 4.5 g/100 mL; OCTOCRYLENE 2.6 g/100 mL
INACTIVE INGREDIENTS: PHENOXYETHANOL; PALMITOYL PENTAPEPTIDE-4; WATER; GLYCERIN; NIACINAMIDE; DIMETHICONE; ISOPROPYL ISOSTEARATE; PANTHENOL; DIMETHICONOL (50000 CST); HYDROXYETHYL ACRYLATE/SODIUM ACRYLOYLDIMETHYL TAURATE COPOLYMER (100000 MPA.S AT 1.5%); 1,2-HEXANEDIOL; BEHENYL ALCOHOL; STEARYL ALCOHOL; CETYL ALCOHOL; CETEARYL GLUCOSIDE; CETEARYL ALCOHOL; STEARIC ACID; PEG-100 STEARATE; EDETATE DISODIUM; STARCH, CORN; CAPRYLYL GLYCOL; PALMITIC ACID

Olay® Regenerist® Regenerating Moisturizer
Broad Spectrum SPF 15

Drug Facts

ACTIVE INGREDIENT

Active ingredients | Purpose
Avobenzone 3.0% | Sunscreen
Homosalate 4.0% | Sunscreen
Octisalate 4.5% | Sunscreen
Octocrylene 2.6% | Sunscreen

Uses

- helps prevent sunburn
- if used as directed with other sun protection measures (see Directions), decreases the risk of skin cancer and early skin aging caused by the sun

Warnings

For external use only

Do not use on damaged or broken skin

When using this product keep out of eyes. Rinse with water to remove.

Stop use and ask a doctor if rash occurs

Keep out of reach of children. If product is swallowed, get medical help or contact a Poison Control Center right away.

Directions

- apply liberally 15 minutes before sun exposure
- reapply at least every 2 hours
- use water resistant sunscreen if swimming or sweating
- Sun Protection Measures. Spending time in the sun increases your risk of skin cancer and early skin aging. To decrease this risk, regularly use a sunscreen with a Broad Spectrum SPF value of 15 or higher and other sun protection measures including:
  - limit time in sun, especially from 10 a.m. - 2 p.m.
  - wear long-sleeved shirts, pants, hats, and sunglasses
- children under 6 months: ask a doctor

Other information

- protect this product from excessive heat and direct sun

Inactive ingredients

water, glycerin, niacinamide*, dimethicone, zea mays (corn) starch, isopropyl isostearate, panthenol**, palmitoyl pentapeptide-4***, caprylyl glycol, dimethiconol, cetearyl glucoside, cetearyl alcohol, stearic acid, palmitic acid, stearyl alcohol, cetyl alcohol, behenyl alcohol, disodium EDTA, hydroxyethyl acrylate/sodium acryloyldimethyl taurate copolymer, PEG-100 stearate, 1,2-hexanediol, phenoxyethanol, fragrance

Questions or comments?

Call 1-800-285-5170

Distr. by PROCTER & GAMBLE,
CINCINNATI, OH 45202

PRINCIPAL DISPLAY PANEL - 75 mL Bottle Carton

OLAY®

REGENERIST®

REGENERATING LOTION

WITH SUNSCREEN BROAD

SPECTRUM SPF 15

ADVANCED FACIAL

ANTI-AGING

MOISTURIZE

BROAD SPECTRUM SPF 15
75 mL (2.5 FL OZ)